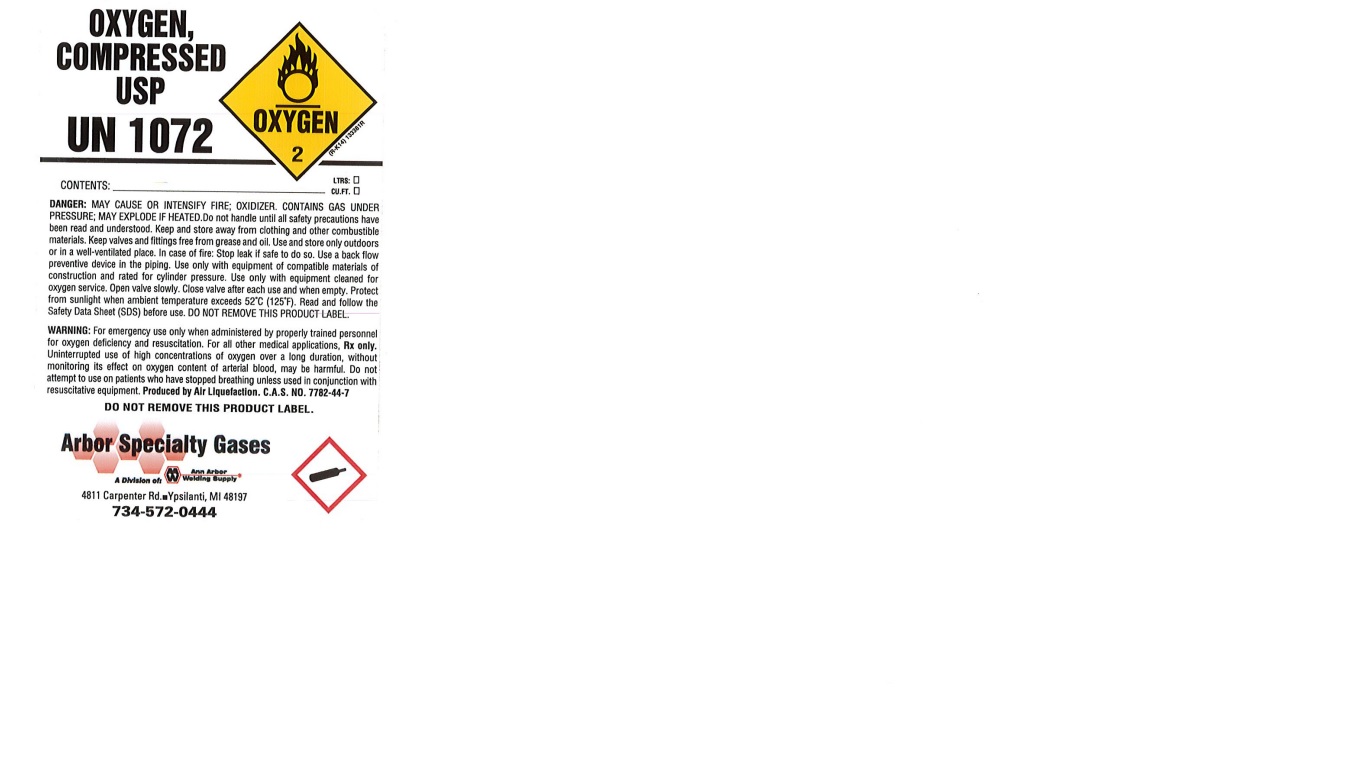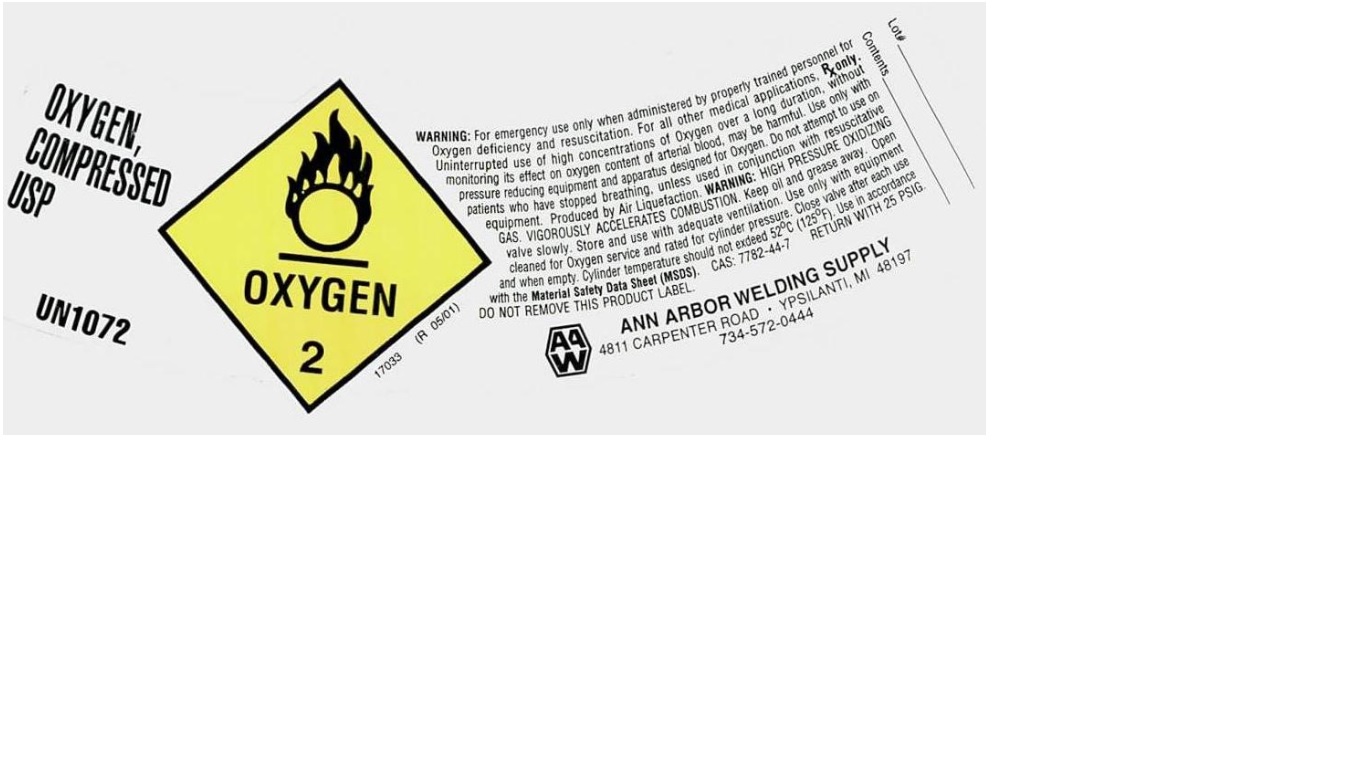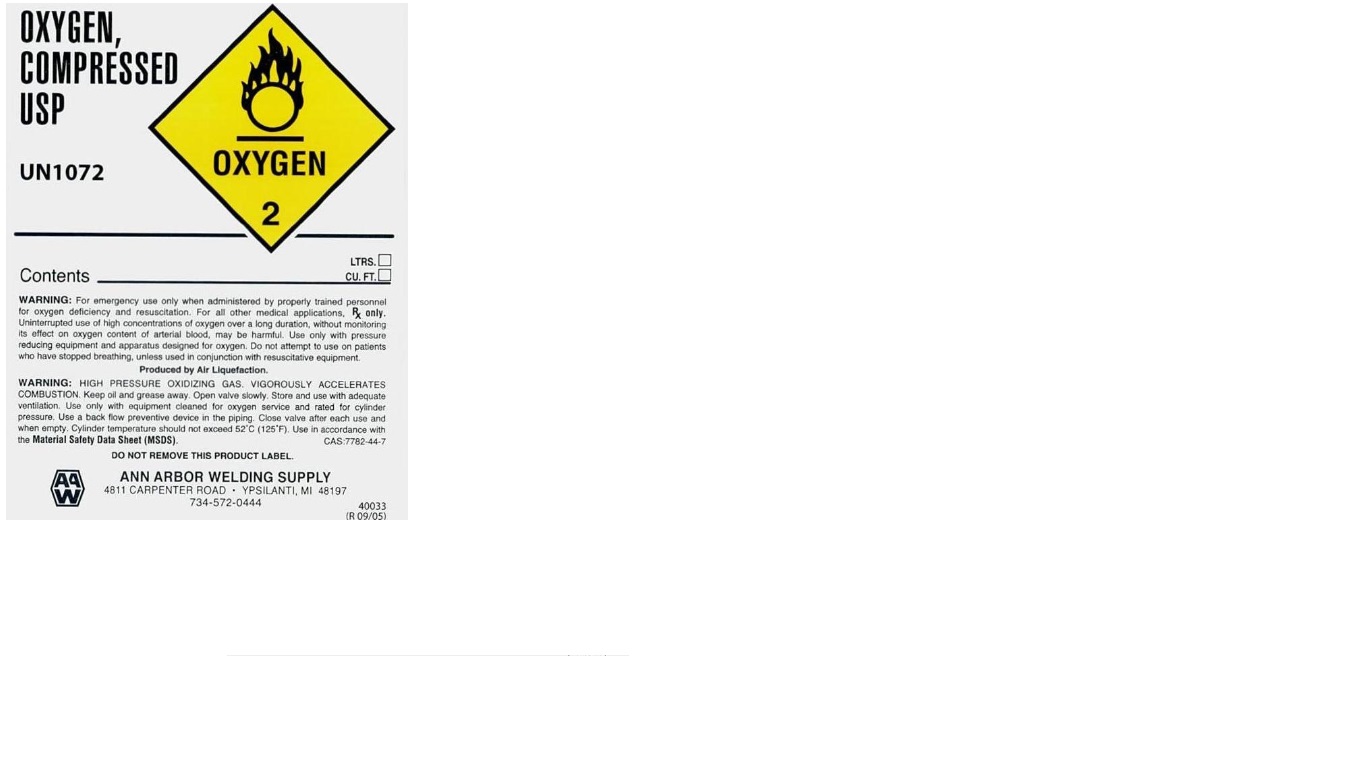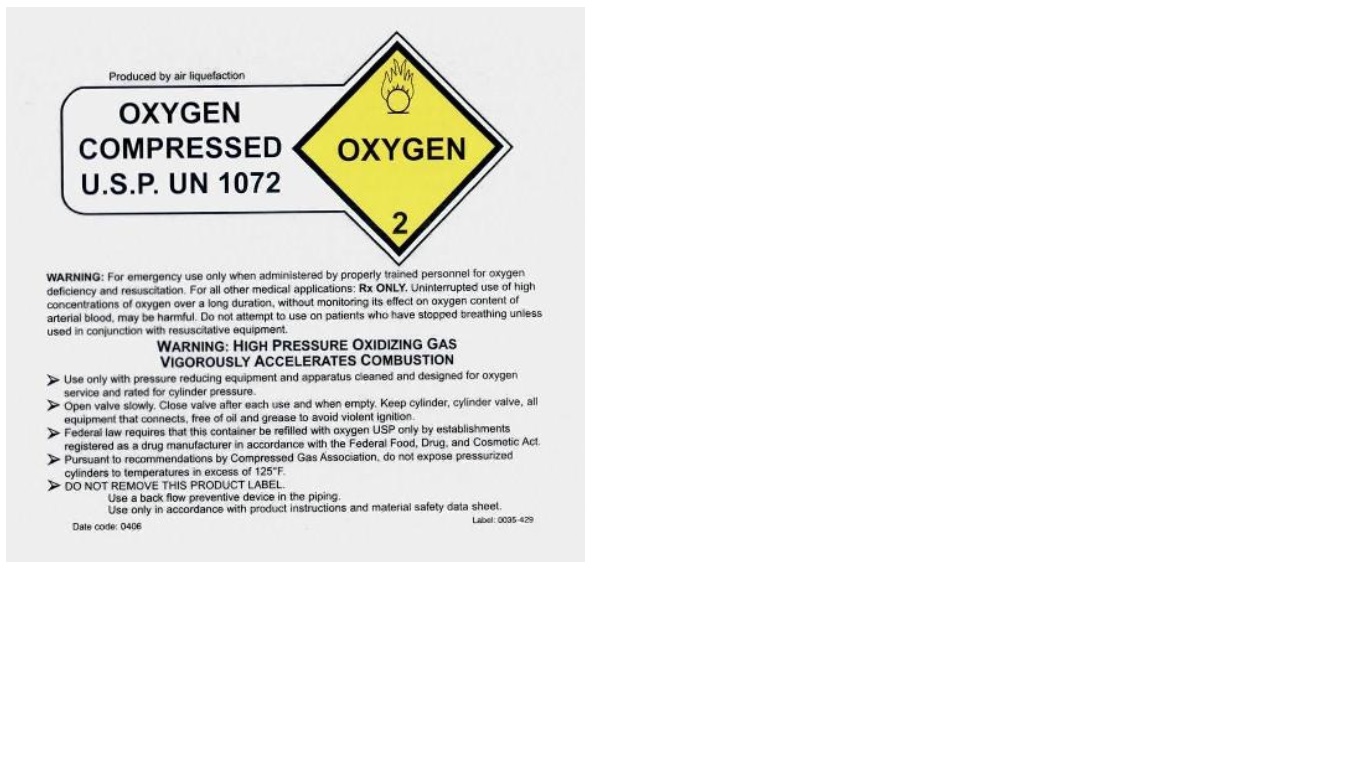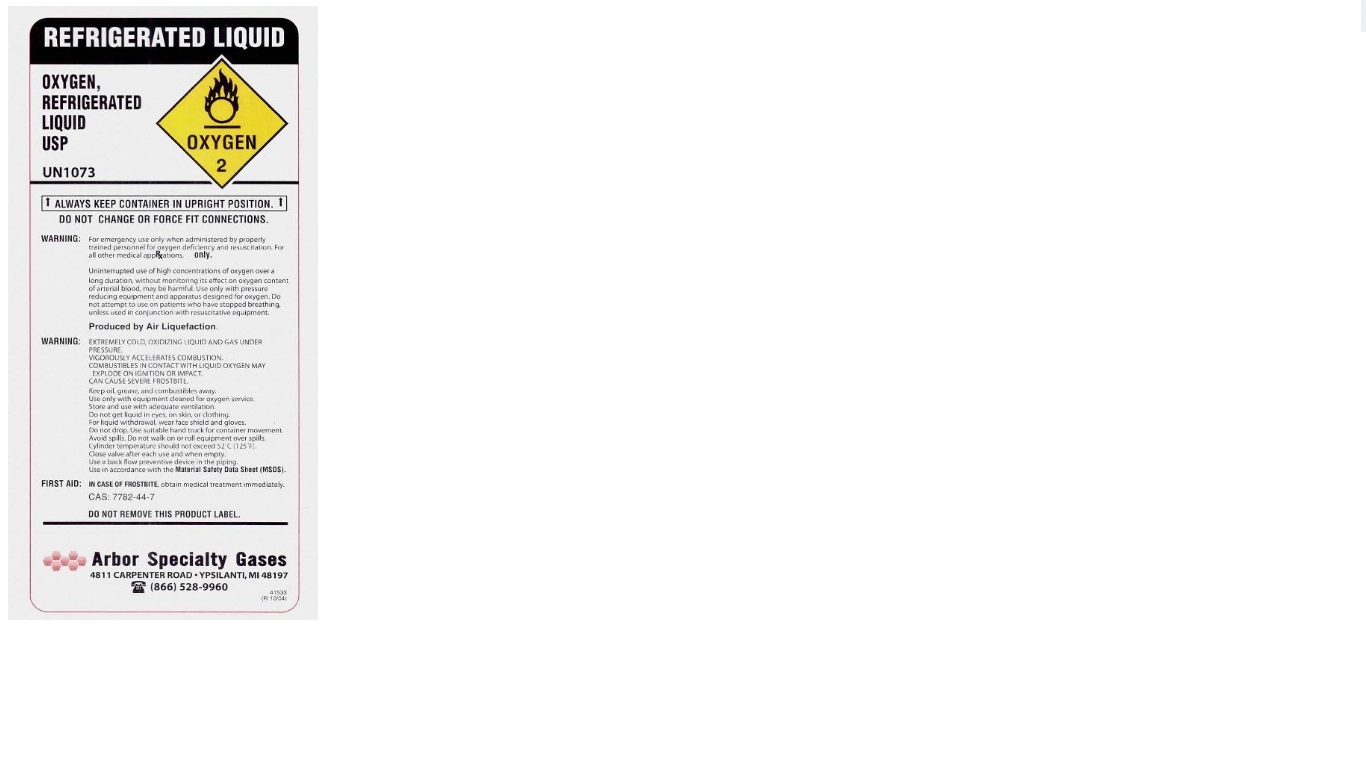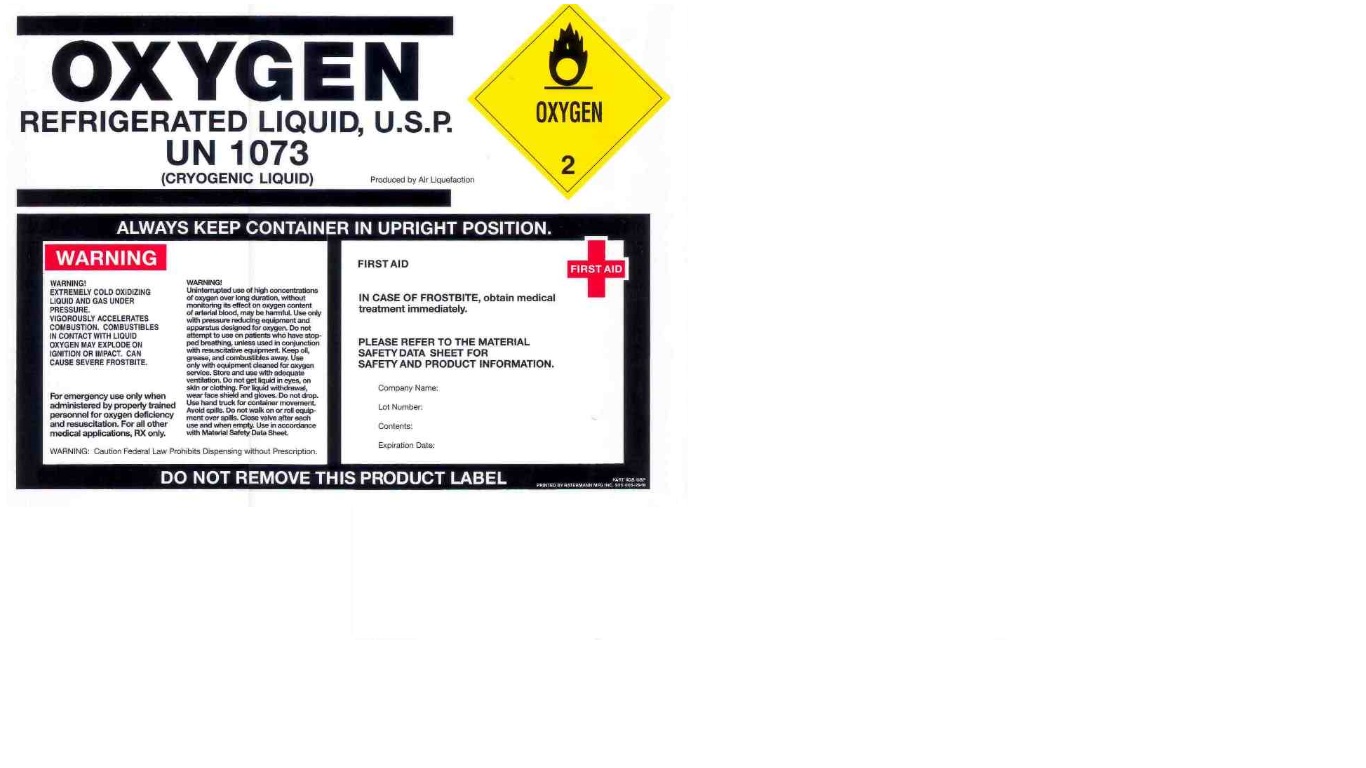 DRUG LABEL: Oxygen
NDC: 59713-001 | Form: GAS
Manufacturer: Ann Arbor Welding Supply Co., Inc. DBA Arbor Specialty Gases
Category: prescription | Type: HUMAN PRESCRIPTION DRUG LABEL
Date: 20211001

ACTIVE INGREDIENTS: OXYGEN 990 mL/1 L

Oxygen Label

PACKAGE LABEL

OXYGEN, COMPRESSED USP
UN 1072
WARNING: For emergency use only when administered by properly trained personnel for Oxygen deficiency and resuscitation. For all other medical applications, Rx only. Uninterrupted use of high concentrations of Oxygen over a long duration, without monitoring its effect on oxygen content of arterial blood, may be harmful. Use only with pressure reducing equipment and apparatus designed for Oxygen. Do not attempt to use on patients who have stopped breathing, unless used in conjuncation with resuscitative equipment. Produced by Air Liquefaction. WARNING: HIGH PRESSURE OXIDIZING GAS. VIGOROUSLY ACCELERATES COMBUSTION. Keep oil and grease away. Open valve slowly. Store and use with adequate ventilation. Use only with equipment cleaned for Oxygen service and rated for cylinder pressure. Close valve after each use and when empty. Cylinder temperature should not exceed 52 C (125 F). Use in accordance with the Material Safety Data Sheet (MSDS). CAS: 7782-44-7. RETURN WITH 25 PSIG. DO NOT REMOVE THIS PRODUCT LABEL.
ANN ARBOR WELDING SUPPLY
4811 CARPENTER ROAD. YPSILANIT, MI 48197
734-572-0444

PACKAGE LABEL

OXYGEN, COMPRESSED USP
UN 1072
Contents LTRS CU.FT.
WARNING: For emergency use only when administered by properly trained personnel for Oxygen deficiency and resuscitation. For all other medical applications, Rx only. Uninterrupted use of high concentrations of Oxygen over a long duration, without monitoring its effect on oxygen content of arterial blood, may be harmful. Use only with pressure reducing equipment and apparatus designed for Oxygen. Do not attempt to use on patients who have stopped breathing, unless used in conjunction with resuscitative equipment. Produced by Air Liquefaction. WARNING: HIGH PRESSURE OXIDIZING GAS. VIGOROUSLY ACCELERATES COMBUSTION. Keep oil and grease away. Open valve slowly. Store and use with adequate ventilation. Use only with equipment cleaned for Oxygen service and rated for cylinder pressure. Close valve after each use and when empty. Cylinder temperature should not exceed 52 C (125 F). Use in accordance with the Material Safety Data Sheet (MSDS). CAS: 7782-44-7. DO NOT REMOVE THIS PRODUCT LABEL.
ANN ARBOR WELDING SUPPLY
4811 CARPENTER ROAD. YPSILANIT, MI 48197
734-572-0444

PACKAGE LABEL

Produced by air liquefaction
OXYGEN, COMPRESSED USP
UN 1072
WARNING: For emergency use only when administered by properly trained personnel for Oxygen deficiency and resuscitation. For all other medical applications, Rx only. Uninterrupted use of high concentrations of Oxygen over a long duration, without monitoring its effect on oxygen content of arterial blood, may be harmful. Do not attempt to use on patients who have stopped breathing, unless used in conjunction with resuscitative equipment. Produced by Air Liquefaction. WARNING: HIGH PRESSURE OXIDIZING GAS. VIGOROUSLY ACCELERATES COMBUSTION. Use only with pressure reducing equipment and apparatus designed for Oxygen. Open valve slowly. Close valve after each use and when empty. Keep cylinder, cylinder valve, all equipment that connects, free of oil and grease to avoid violent ignition. Federal law requires that this container be refilled with oxygen USP only be establishments registered as a drug manufacturer in accordance with the Federal Food, Drug, and Cosmetic Act. Pursuant to recommendations by Compressed Gas Association, do not expose pressured cylinders to temperatures in excess of 125 F. DO NOT REMOVE THIS PRODUCT LABEL. Use a back flow preventive device in the piping. Use only in accordance with product instructions and Material Safety Data Sheet.

PACKAGE LABEL

REFRIGERATED LIQUID
OXYGEN, REFRIGERATED LIQUID USP UN1073
ALWAYS KEEP CONTAINER IN UPRIGHT POSITION DO NOT CHANGE OR FORCE FIT CONNECTIONS.
WARNING: For emergency use only when administered by properly trained personnel for oxygen deficiency and resuscitation. For all other medical applications, Rx Only.
Uninterrupted use of high concentrations of oxygen over a long duration, without monitoring its effect on oxygen content of arterial blood, may be harmful. Use only with pressure reducing equipment and apparatus designed for oxygen. Do not attempt to use on patients who have stopped breathing, unless used in conjunction with resuscitative equipment.
Produced by Air Liquefaction.
WARNING: EXTREMELY COLD, OXIDIZING LIQUID AND GAS UNDER PRESSURE. VIGOROUSLY ACCELERATES COMBUSTION. COMBUSTIBLES IN CONTACT WITH LIQUID OXYGEN MAY EXPLODE ON IGNITION OR IMPACT. CAN CAUSE SEVERE FROSTBITE. Keep oil, grease, and combustibles away. Use only with equipment cleaned for oxygen service. Store and use with adequate ventilation. Do not get liquid in eyes, on skin, or clothing. For liquid withdrawal, wear face shield and gloves. Do not drop. Use suitable hand truck for container movement. Avoid spills. Do not walk on or roll equipment over spills. Cylinder temperature should not exceed 52 C (125 F). Close valve after each use and when empty. Use a back flow preventive device in the piping. Use in accordance with the Material Safety Data Sheet (MSDS). FIRST AID: IN CASE OF FROSTBITE, obtain medical treatment immediately. CAS: 7782-44-7
DO NOT REMOVE THIS PRODUCT LABEL.
Arbor Specialty Gases
4811 CARPENTER ROAD. YPSILANTI, MI 48197
866-528-9960

PACKAGE LABEL

OXYGEN, REFRIGERATED LIQUID USP UN1073 (CRYOGENIC LIQUID) Produced by Air Liquefaction
ALWAYS KEEP CONTAINER IN UPRIGHT POSITION
WARNING: WARNING: EXTREMELY COLD, OXIDIZING LIQUID AND GAS UNDER PRESSURE. VIGOROUSLY ACCELERATES COMBUSTION. COMBUSTIBLES IN CONTACT WITH LIQUID OXYGEN MAY EXPLODE ON IGNITION OR IMPACT. CAN CAUSE SEVERE FROSTBITE. For emergency use only when administered by properly trained personnel for oxygen deficiency and resuscitation. For all other medical applications, Rx Only. WARNING! Uninterrupted use of high concentrations of oxygen over a long duration, without monitoring its effect on oxygen content of arterial blood, may be harmful. Use only with pressure reducing equipment and apparatus designed for oxygen. Do not attempt to use on patients who have stopped breathing, unless used in conjunction with resuscitative equipment. Keep oil, grease, and combustibles away. Use only with equipment cleaned for oxygen service. Store and use with adequate ventilation. Do not get liquid in eyes, on skin, or clothing. For liquid withdrawal, wear face shield and gloves. Do not drop. Use hand truck for container movement. Avoid spills. Do not walk on or roll equipment over spills. Close valve after each use and when empty. Use a back flow preventive device in the piping. Use in accordance with the Material Safety Data Sheet (MSDS). WARNING: Caution Federal Law Prohibits Dispensing without Prescription.
FIRST AID: IN CASE OF FROSTBITE, obtain medical treatment immediately. PLEASE REFER TO THE MATERIAL SAFETY DATA SHEET FOR SAFETY AND PRODUCT INFORMATION.
Company Name:
Lot Number:
Contents:
Expiration Date:
DO NOT REMOVE THIS PRODUCT LABEL.

PACKAGE LABEL

OXYGEN, COMPRESSED USP

UN 1072

CONTENTS: LTRS: CU. FT.

DANGER: MAY CAUSE OR INTENSIFY FIRE; OXIDIZER. CONTAINS GAS UNDER PRESSURE; MAY EXPLODE IF HEATED. Do not handle until all safety precautions have been read and understood. Keep and store away from clothing and other combustible materials. Keep valves and fittings free from grease and oil. Use and store only outdoors or in a well-ventilated place. In case of fire: Stop leak if safe to do so. Use a back flow preventive device in the piping. Use only with equipment of compatible materials of construction and rated for cylinder pressure. Use only with equipment cleaned for oxygen service. Open valve slowly. Close valve after each use and when empty. Protect from sunlight when ambient temperature exceeds 52 C (125 F). Read and follow the Safety Data Sheet (SDS) before use. DO NOT REMOVE THIS PRODUCT LABEL.

WARNING: For emergency use only when administered by properly trained personnel for oxygen deficiency and resuscitation. For all other medical applications, Rx only. Uninterrupted use of high concentrations of oxygen over a long duration, without monitoring its effect on oxygen content of arterial blood, may be harmful. Do not attempt to use on patients who have stopped breathing unless used in conjunction with resuscitative equipment. Produced by Air Liquefaction. C.A.S. NO. 7782-44-7

DO NOT REMOVE THIS PRODUCT LABEL.

Arbor Specialty Gases

A Division of: Ann Arbor Welding Supply

4811 Carpenter Rd. Ypsilanti, MI 48197

734-572-0444